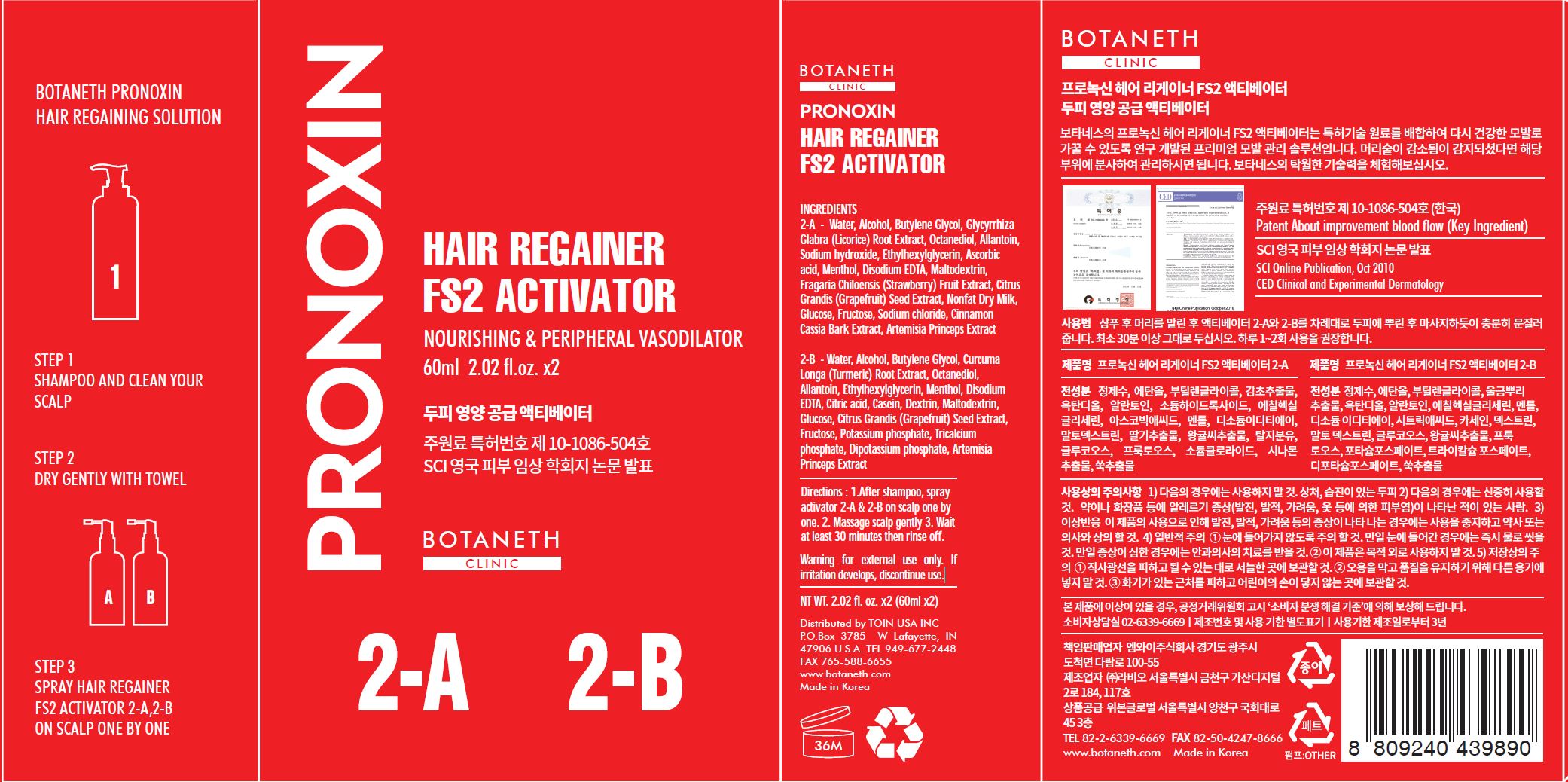 DRUG LABEL: BOTANETH PRONOXIN HAIR REGAINER FS2 ACTIVATOR 2-A 2-B
NDC: 73199-0002 | Form: KIT | Route: TOPICAL
Manufacturer: OUIBON GLOBAL
Category: otc | Type: HUMAN OTC DRUG LABEL
Date: 20190713

ACTIVE INGREDIENTS: ALLANTOIN 0.1 g/100 mL; ALLANTOIN 0.1 g/100 mL
INACTIVE INGREDIENTS: WATER; WATER

Drug Facts

ACTIVE INGREDIENT

ALLANTOIN

INACTIVE INGREDIENT

2-A - Water, Alcohol, Butylene Glycol, Glycyrrhiza
Glabra (Licorice) Root Extract, Octanediol, Allantoin,
Sodium hydroxide, Ethylhexylglycerin, Ascorbic
acid, Menthol, Disodium EDTA, Maltodextrin,
Fragaria Chiloensis (Strawberry) Fruit Extract, Citrus
Grandis (Grapefruit) Seed Extract, Nonfat Dry Milk,
Glucose, Fructose, Sodium chloride, Cinnamon
Cassia Bark Extract, Artemisia Princeps Extract

2-B - Water, Alcohol, Butylene Glycol, Curcuma
Longa (Turmeric) Root Extract, Octanediol,
Allantoin, Ethylhexylglycerin, Menthol, Disodium
EDTA, Citric acid, Casein, Dextrin, Maltodextrin,
Glucose, Citrus Grandis (Grapefruit) Seed Extract,
Fructose, Potassium phosphate, Tricalcium
phosphate, Dipotassium phosphate, Artemisia
Princeps Extract

PURPOSE

Protect scalp, hair loss prevention

keep out of reach of the children

INDICATIONS AND USAGE

1.After shampoo, spray activator 2-A & 2-B on scalp one by one.

2. Massage scalp gently 3. Wait at least 30 minutes then rinse off.

WARNINGS

for external use only. If irritation develops, discontinue use.

DOSAGE AND ADMINISTRATION

for topical use only